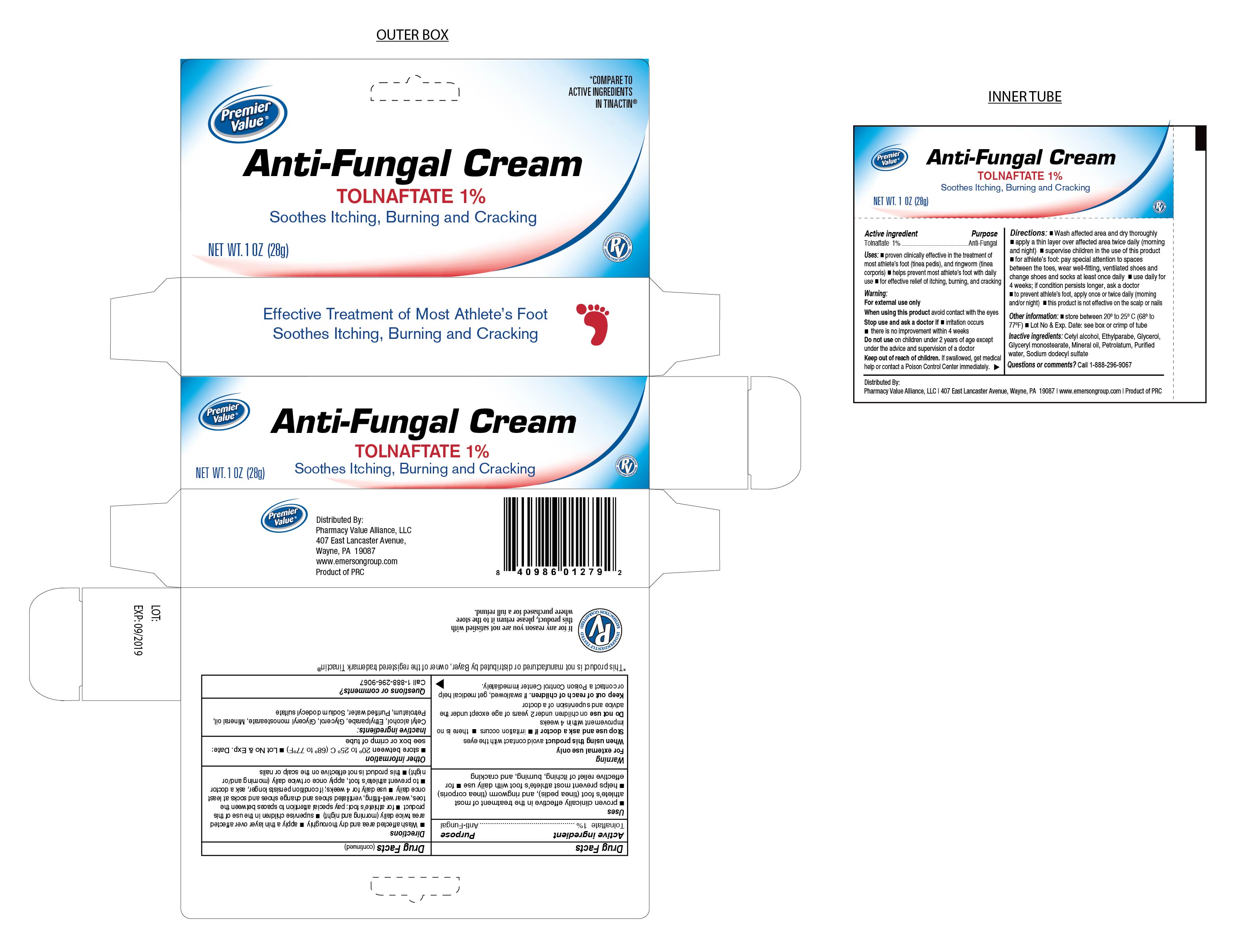 DRUG LABEL: Tolnaftate Cream 1%
NDC: 68016-152 | Form: CREAM
Manufacturer: Pharmacy Value Alliance, LLC.
Category: otc | Type: HUMAN OTC DRUG LABEL
Date: 20241220

ACTIVE INGREDIENTS: TOLNAFTATE 10 mg/1 g
INACTIVE INGREDIENTS: CETOSTEARYL ALCOHOL; STEARYL ALCOHOL; LIGHT MINERAL OIL; SODIUM LAURYL SULFATE; WATER; ETHYLPARABEN; GLYCERYL MONOSTEARATE; PETROLATUM; GLYCERIN

Tolnaftate Cream 1%

Active Ingredient

Tolnaftate 1%

Purpose

Anti-Fungal

Uses

- Proven clinically effective in the treatment of most athlete's foot (tinea pedis), and ringworm (tinea corporis)
- Helps prevent most athlete's foot with daily use
- For effective relief of itching, burning, and cracking

Keep out of the reach of children

If swallowed, get medical help or contact a Poison Control Center immediately.

Warnings

For External Use Only

When using this product avoid contact with the eyes

Do not use on children under 2 years of age except under the advice and supervision of a doctor

Directions

- Wash affected area and dry thoroughly
- Apply a thin layer over affected area twice daily (morning and night)
- Supervise children in the use of this product
- for athlete's foot: pay special attention to spaces between the toes, wear well-fitting, ventilated shoes and change shoes and socks at least once daily
- Use daily for 4 weeks; if condition persists longer, ask a doctor
- To prevent athlete's foot, apply once or twice daily (morning and/or night)
- This product is not effective on the scalp or nails

Stop use and ask a doctor if

- irritation occurs
- there is no improvement within 4 weeks

Other Information

- Store between 20° to 25°C (68° to 77°F)
- Lot No & Expiration Date: See box or crimp of tube

Inactive ingredients:

Cetyl alcohol, Ethylparabe, Glycerol, Glyceryl Monostearate, Mineral Oil, Petrolatum, Purified Water, Sodium Dodecyl sulfate

Soothes Itching, Burning and Cracking

Distributed By:

Pharmacy Value Alliance, LLC.

407 East Lancaster Avenue, Wayne, PA. 19087 USA

www.emersongroup.com